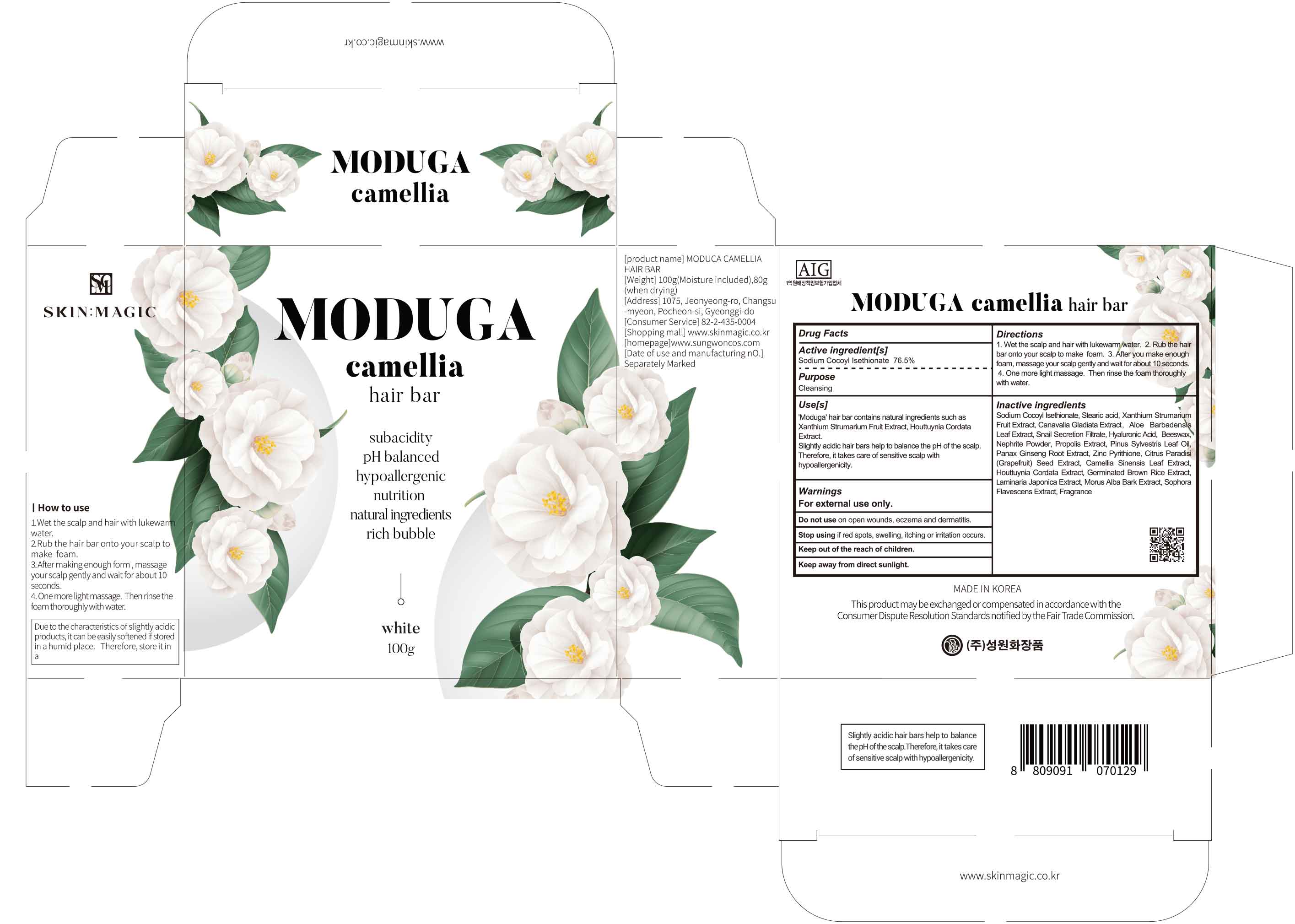 DRUG LABEL: MODUGA camellia hair bar
NDC: 74721-0070 | Form: SOAP
Manufacturer: S-ONE PHARMACEUTICAL INC
Category: otc | Type: HUMAN OTC DRUG LABEL
Date: 20230126

ACTIVE INGREDIENTS: SODIUM COCOYL ISETHIONATE 76.5 g/100 g
INACTIVE INGREDIENTS: STEARIC ACID; XANTHIUM STRUMARIUM FRUIT; CANAVALIA GLADIATA SEED POD; ALOE VERA LEAF; HYALURONIC ACID; YELLOW WAX; PROPOLIS WAX; PINE NEEDLE OIL (PINUS SYLVESTRIS); ASIAN GINSENG; PYRITHIONE ZINC; CITRUS PARADISI SEED; GREEN TEA LEAF; HOUTTUYNIA CORDATA FLOWERING TOP; LAMINARIA JAPONICA; MORUS ALBA BARK; SOPHORA FLAVESCENS ROOT

74721-0070 MODUGA camellia hair bar

Active ingredient[s]

Sodium Cocoyl Isethionate 76.5%

Purpose

Cleansing

Use[s]

'Moduga' hair bar contains natural ingredients such as Xanthium Strumarium Fruit Extract, Houttuynia Cordata Extract.

Slightly acidic hair bars help to balance the pH of the scalp with hypoallergenicity.

Warnings

For external use only.

Do not use

on open wounds, eczema and dermatitis.

Stop using

if red spots, swelling, itching or irritation occurs.

Keep out of the reach of children.

Other information

Keep out of the reach of children.

Directions

1. Wet the scalp and hair with lukewarm water.
2. Rub the hair bar onto your scalp to make foam.
3. After making enough form, Massage your scalp gently and wait for about 10 seconds.
4. One more light massage. Then rinse the foam thoroughly with water.

Inactive ingredients

Sodium Cocoyl Isethionate, Stearic acid, Xanthium Strumarium Fruit Extract, Canavalia Gladiata Extract, Aloe Barbadensis Leaf Extract,Snail Secretion Filtrate, Hyaluronic Acid, Beeswax, Nephrite Powder, Propolis Extract, Pinus Sylvestris Leaf Oil, Panax Ginseng Root Extract, Zinc Pyrithione, Citrus Paradisi (Grapefruit) Seed Extract, Camellia Sinensis Leaf Extract, Houttuynia Cordata Extract,Germinated Brown Rice Extract, Laminaria Japonica Extract, Morus Alba Bark Extract, Sophora Flavescens Extract, Fragrance